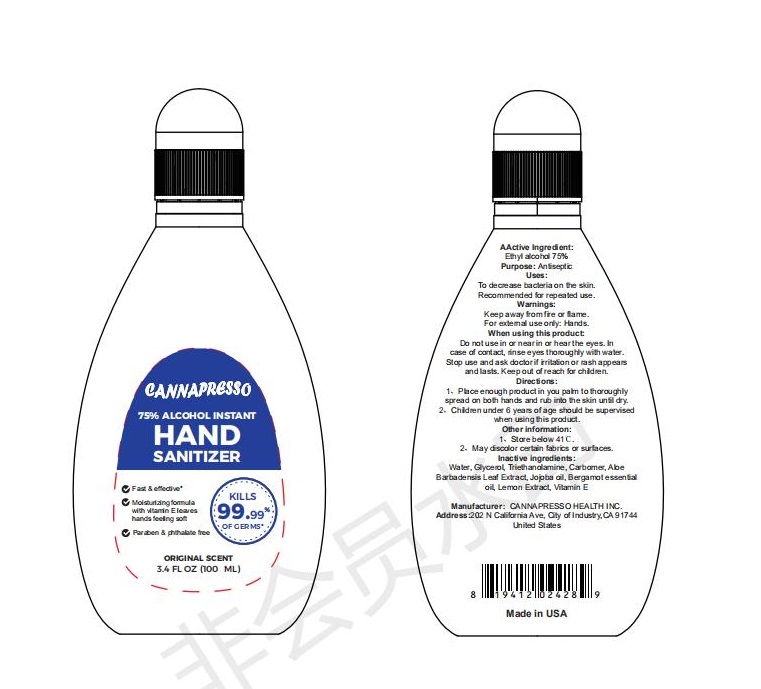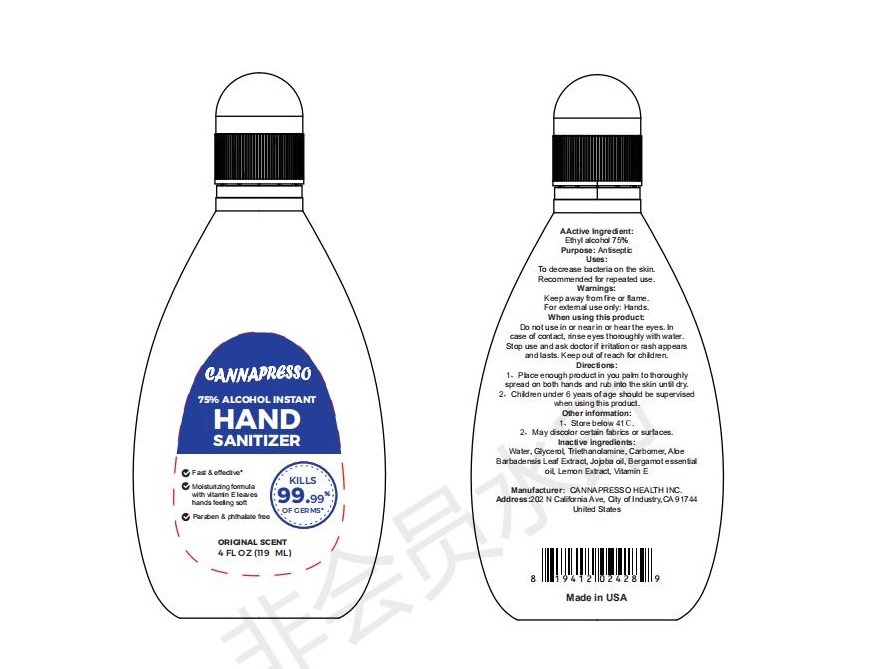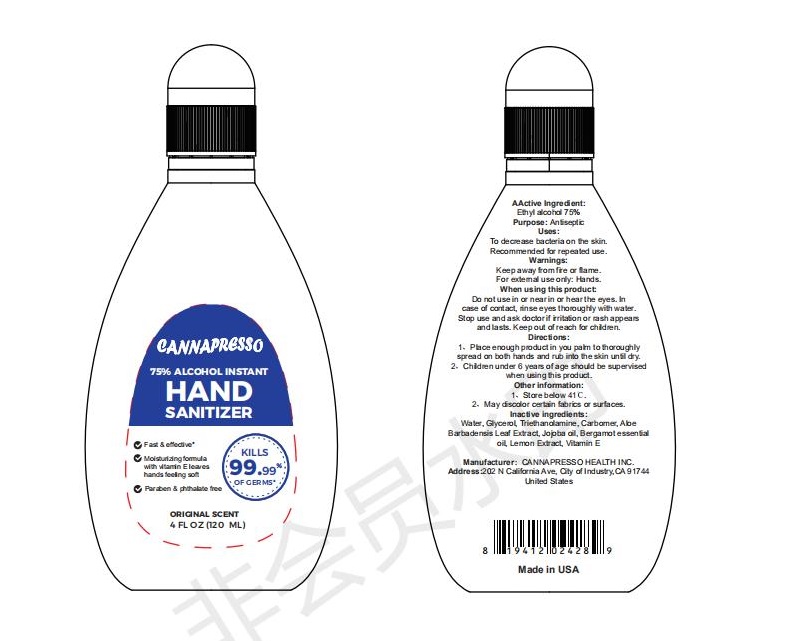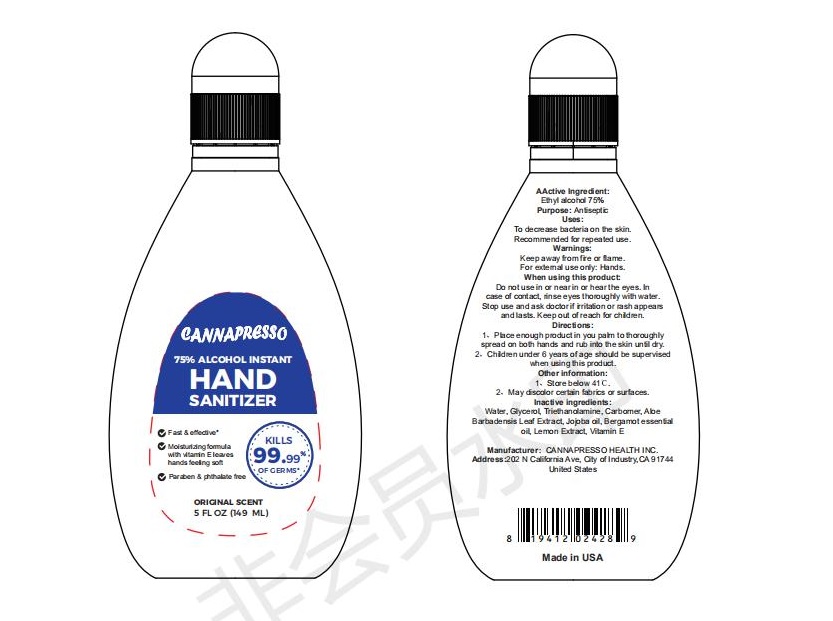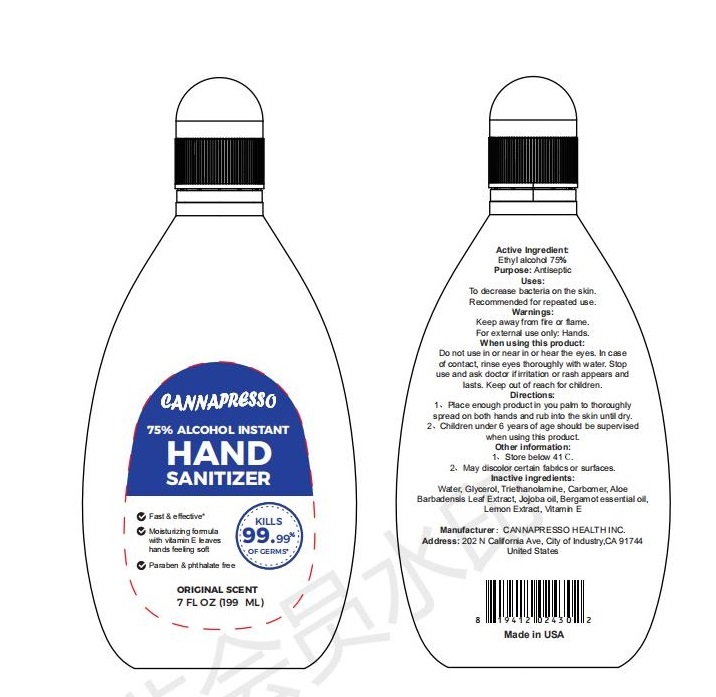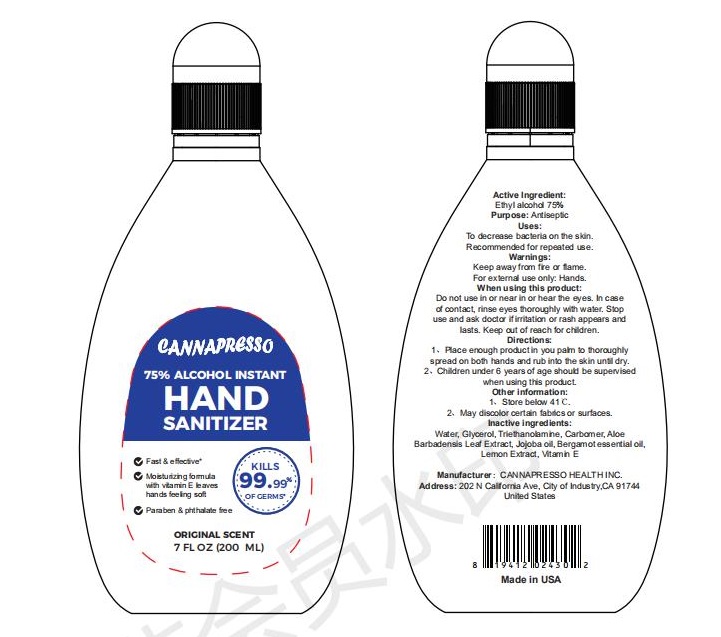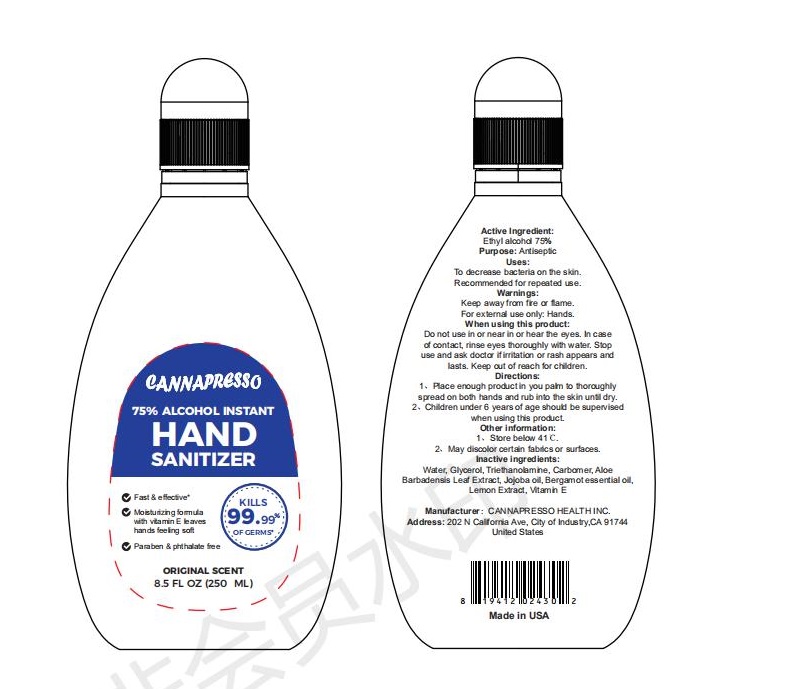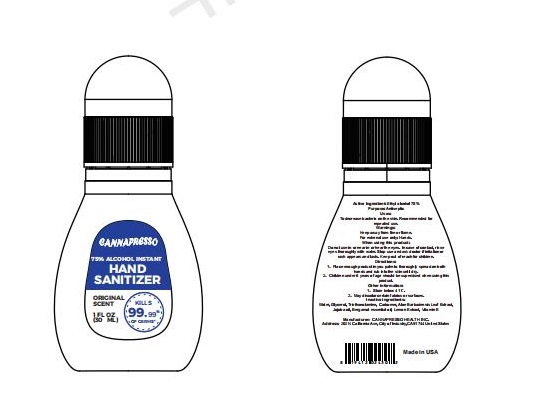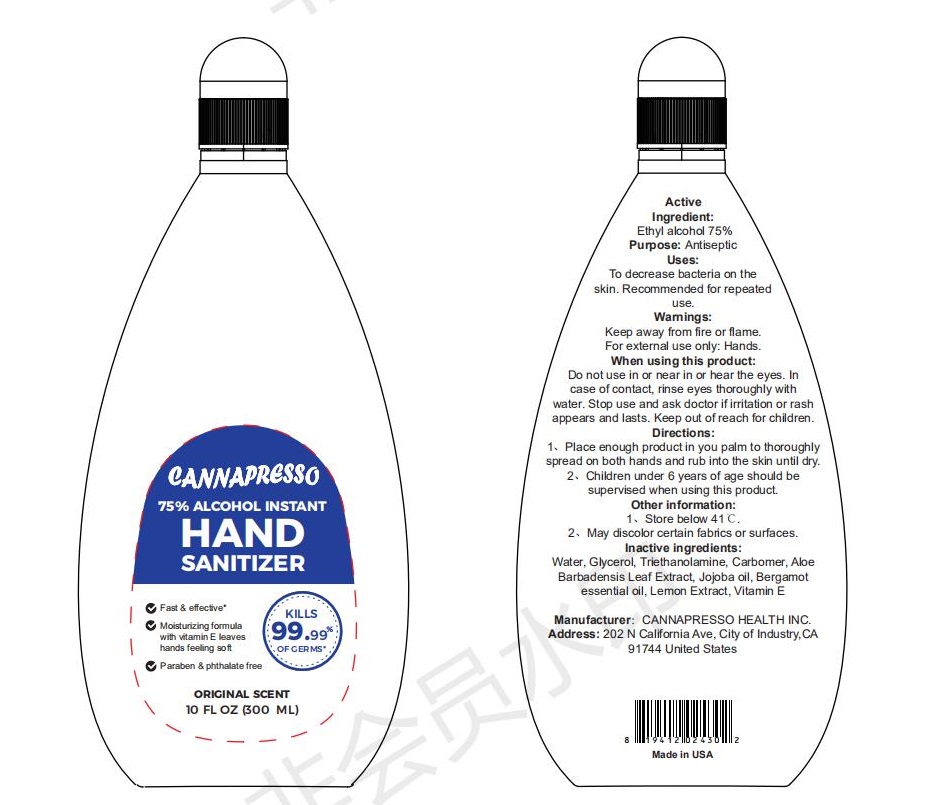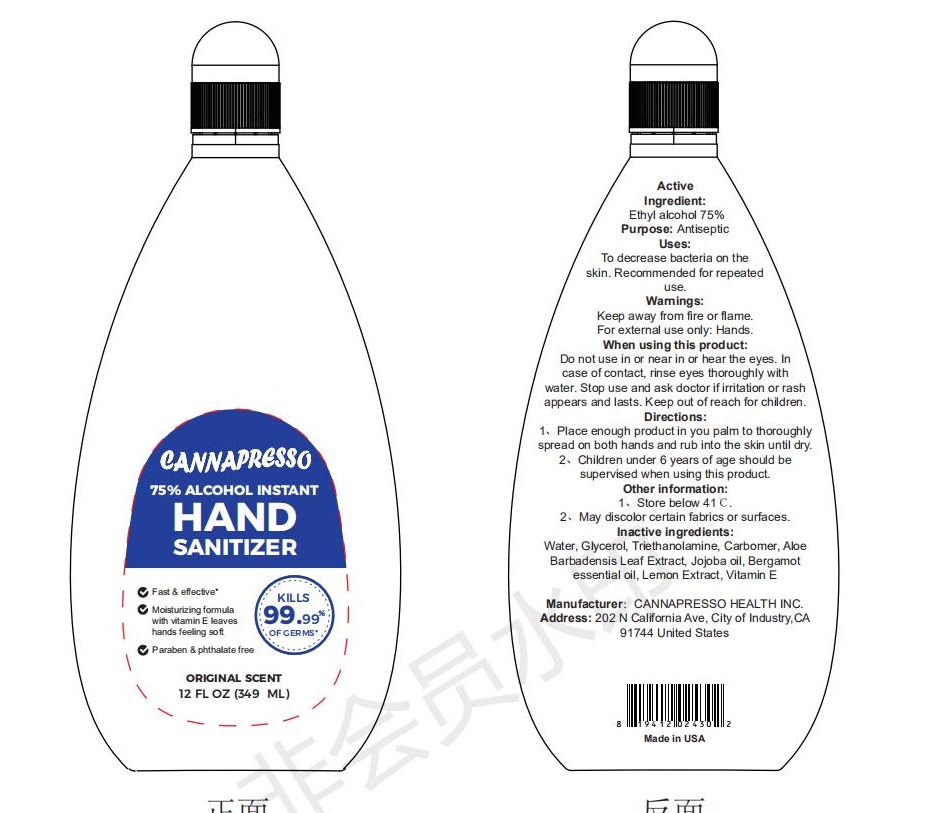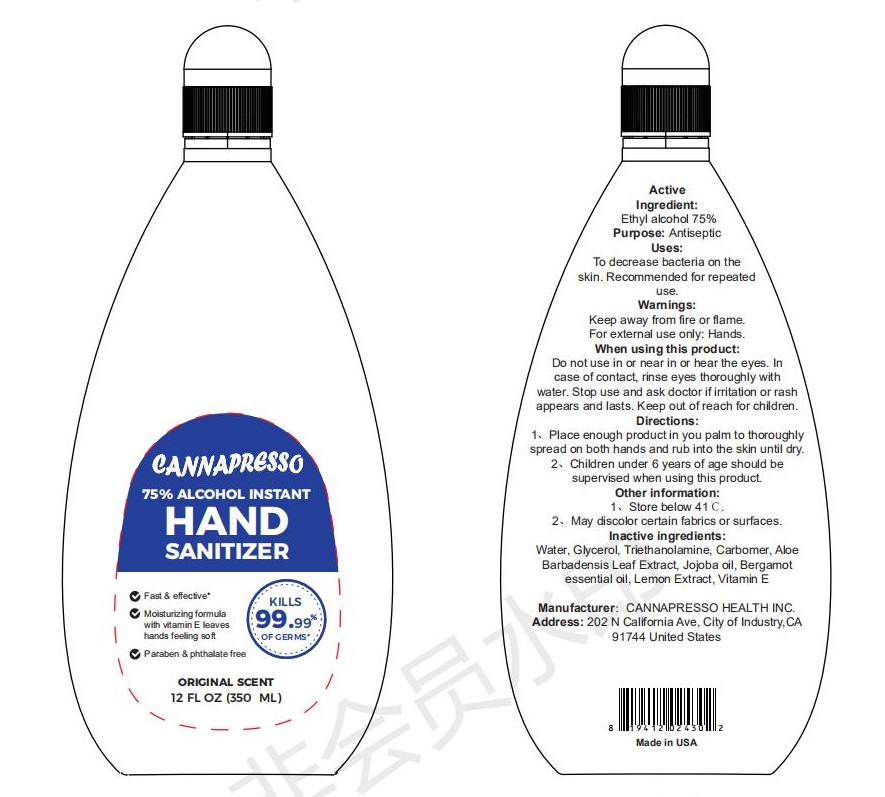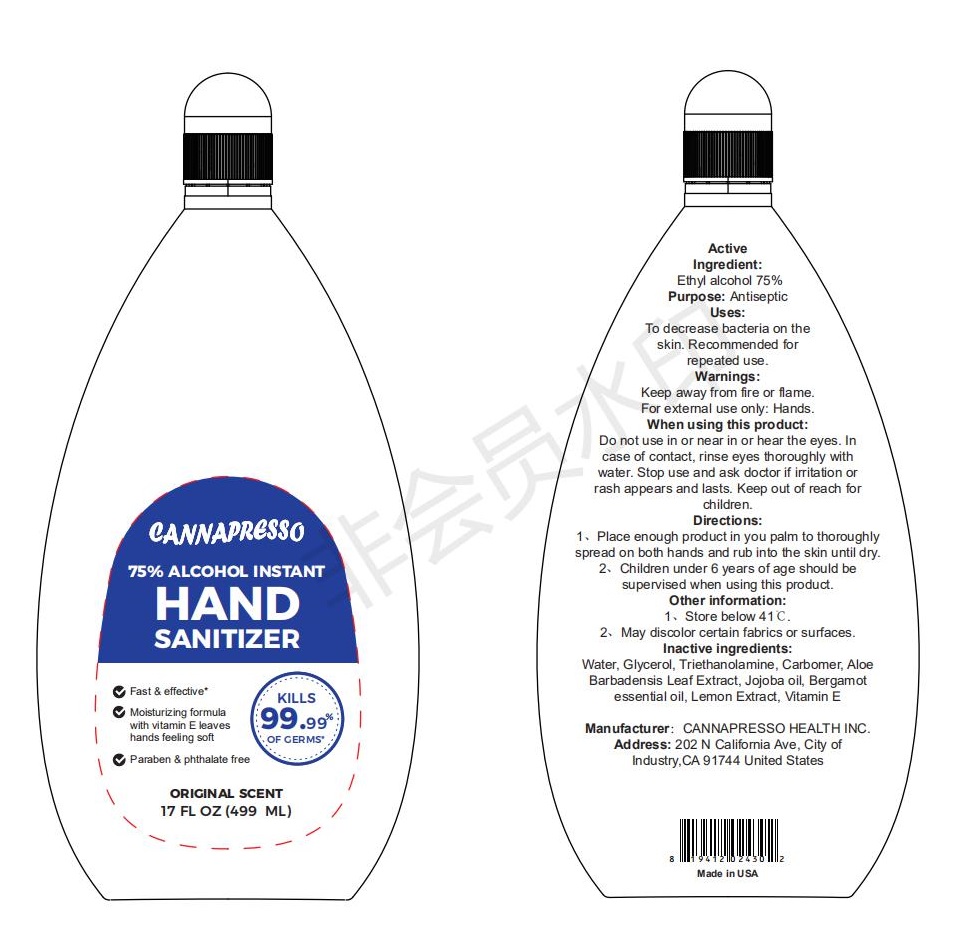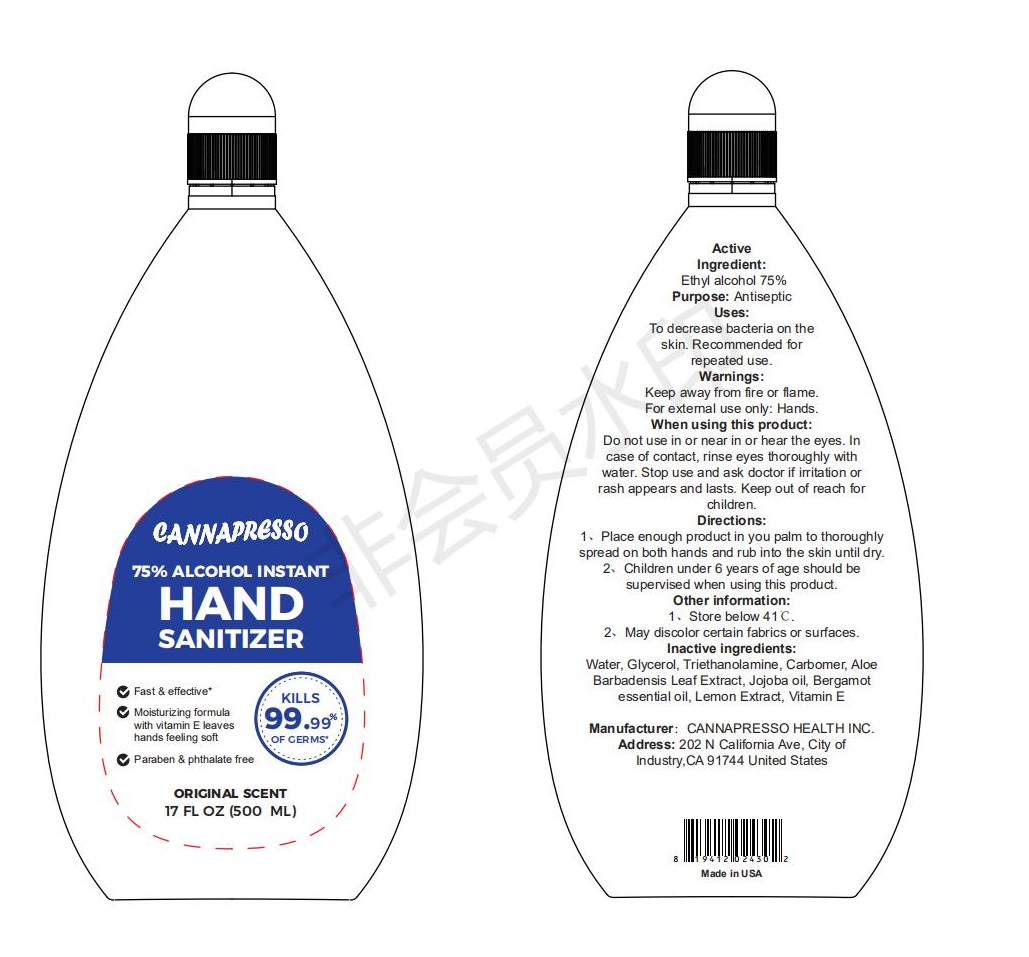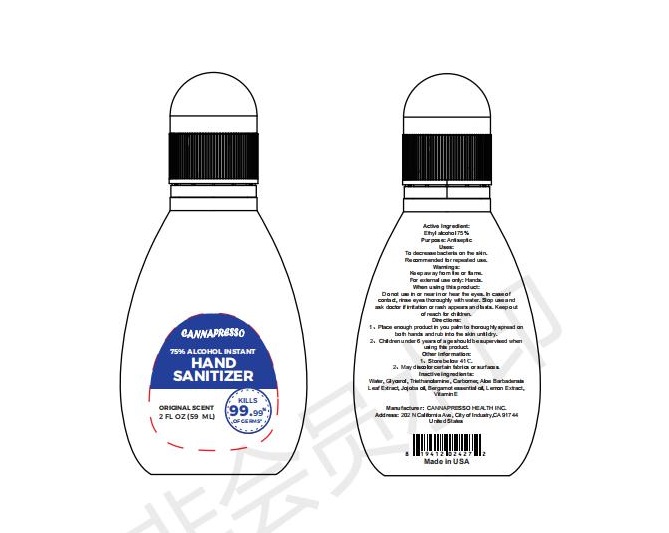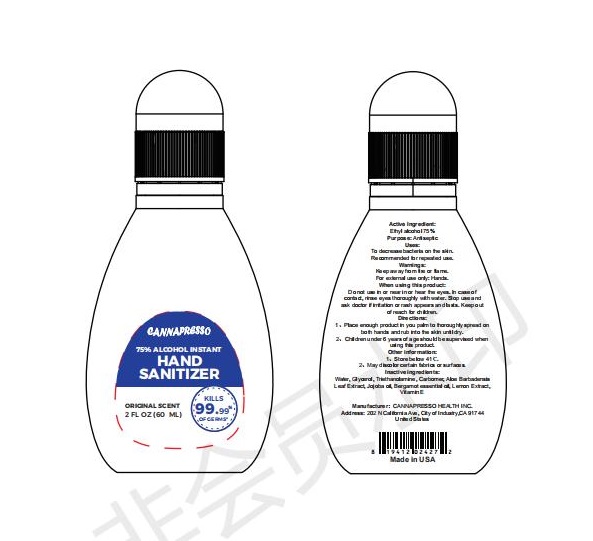 DRUG LABEL: 75% Alchohol Instant Hand Sanitizer
NDC: 75242-005 | Form: GEL
Manufacturer: Cannapresso Health. Inc.
Category: otc | Type: HUMAN OTC DRUG LABEL
Date: 20200414

ACTIVE INGREDIENTS: ALCOHOL 75 mL/100 mL
INACTIVE INGREDIENTS: LEMON 0.025 g/100 mL; TROLAMINE 0.3 g/100 mL; BERGAMOT OIL 0.025 g/100 mL; CARBOMER 934 0.3 g/100 mL; ALPHA-TOCOPHEROL 0.02 g/100 mL; GLYCERIN 5 mL/100 mL; ALOE VERA LEAF 0.025 g/100 mL; WATER; JOJOBA OIL 0.025 g/100 mL

Active Ingredient(s)

Isopropyl Alcohol 75% v/v. Purpose: Antiseptic

Purpose

Antiseptic

Use

TO DECREASE BACTERIA ON THE SKIN ,RECOMMENDED FOR REPEATED USE.

Warnings

KEEP AWAY FROM FIRE OR FLAME.FOR EXTERNAL USE ONLY:HANDS

Do not use

- in children less than 2 months of age
- on open skin wounds

DO NOT USE IN OR NEAR IN OR HEAR THE EYES.IN CASE OF CONTACT,RINSE EYES THOROUGHLY WITH WATER.STOP USE AND ASK DOCTOR IF IRRITATION OR RASH APPEARS AND LASTS. KEEP OUT OF REACH FOR CHILDREN.

Stop use and ask a doctor if irritation or rash occurs. These may be signs of a serious condition.

Keep out of reach of children. If swallowed, get medical help or contact a Poison Control Center right away.

Directions

PLACE ENOUGH PRODUCT IN YOU PALM TO THOROUGHLY SPREAD ON BOTH HANDS AND RUB INTO THE SKIN UNTIL DRY.CHILDREN UNDER 6 YEARS OF AGE SHUOULD BE SUPERVISED WHEN USING THIS PRODUCT.

Other information

STORE BELOW 41C.MAY DISCOLOR CERTAIN FABRICS OR SURFACES.

Inactive ingredients

TROLAMINE,BERGAMOT OIL,CARBOMER 934,JOJOBA OIL,GLYCERIN,

ALOE VERA LEAF,WATER,LEMON,VITAMIN E